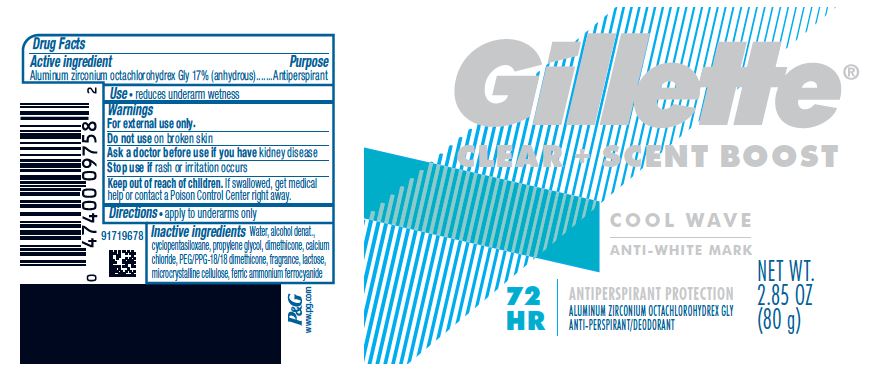 DRUG LABEL: Gillette Clear Plus Scent Boost Cool Wave
NDC: 69423-585 | Form: GEL
Manufacturer: The Procter & Gamble Manufacturing Company
Category: otc | Type: HUMAN OTC DRUG LABEL
Date: 20250225

ACTIVE INGREDIENTS: ALUMINUM ZIRCONIUM OCTACHLOROHYDREX GLY 17 g/100 g
INACTIVE INGREDIENTS: FERRIC AMMONIUM FERROCYANIDE; ANHYDROUS LACTOSE; MICROCRYSTALLINE CELLULOSE; TETRAHYDROLINALOOL; ORANGE TERPENES; DIPROPYLENE GLYCOL; ALLYL AMYL GLYCOLATE; LINALOOL, (+/-)-; BENZYL SALICYLATE; COUMARIN; PROPYLENE GLYCOL; WATER; ALCOHOL; CYCLOMETHICONE 5; DIMETHICONE; CALCIUM CHLORIDE; PEG/PPG-18/18 DIMETHICONE; .BETA.-CITRONELLOL, (R)-; LINALYL ACETATE; CITRONELLYL NITRILE, (+/-)-; HEXAMETHYLINDANOPYRAN; BENZYL BENZOATE; TETRAHYDROLINALYL ACETATE; DIHYDROMYRCENOL; CITRAL

Gillette® Clear Plus Scent Boost Cool Wave

Drug Facts

Active ingredient

Aluminum zirconium octachlorohydrex Gly 17% (anhydrous)

Purpose

Antiperspirant

Use

reduces underarm wetness

Warnings

For external use only.

Do not use on broken skin

Ask a doctor before use if you have kidney disease

Stop use if rash or irritation occurs

Keep out of reach of children. If swallowed, get medical help or contact a Poison Control Center right away.

Directions

- apply to underarms only

Inactive ingredients

Water, alcohol denat., cyclopentasiloxane, propylene glycol, dimethicone, calcium chloride, PEG/PPG-18/18 dimethicone, fragrance, lactose, microcrystalline cellulose, ferric ammonium ferrocyanide

Questions?

1-800-445-5388

Dist. by PROCTER & GAMBLE,
CINCINNATI, OH 45202.

PACKAGE LABEL

Gillette ®
CLEAR + SCENT BOOST

COOL WAVE

ANTI-WHITE MARK

ANTIPERSPIRANT PROTECTION

ALUMINUM ZIRCONIUM OCTACHLOROHYDREX GLY

ANTI-PERSPIRANT/DEODORANT

NET WT. 2.85 OZ (80 g)